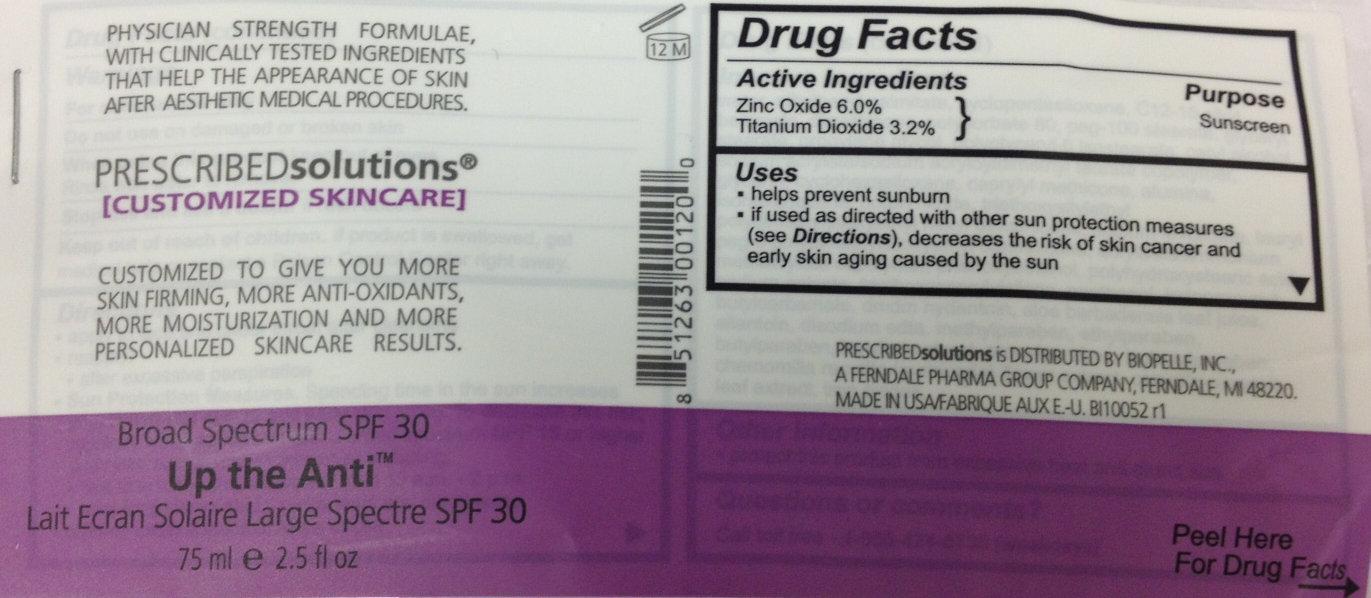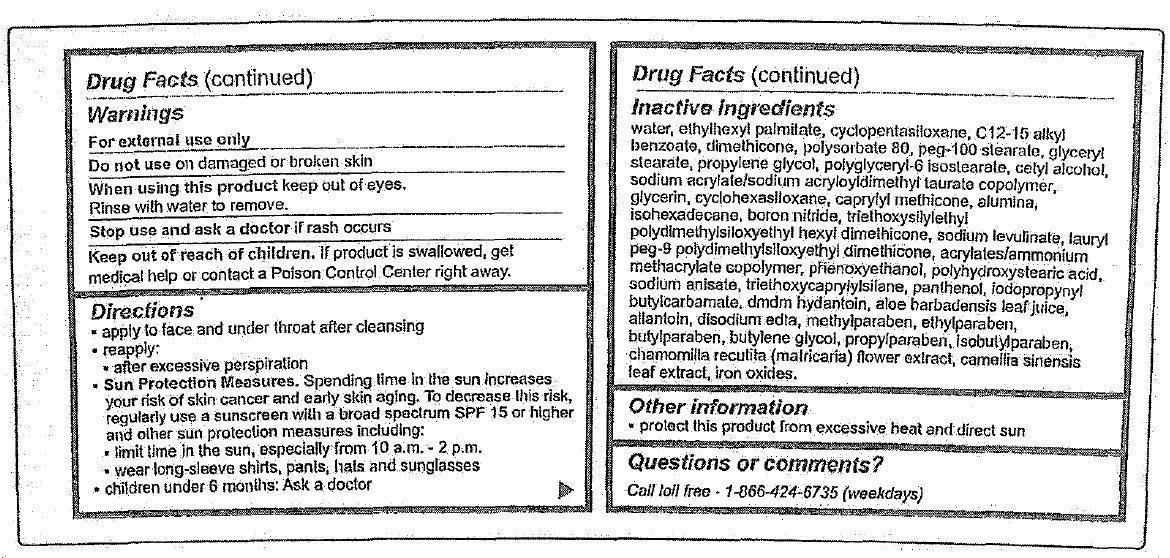 DRUG LABEL: Broad Spectrum SPF 30 Up The Anti
NDC: 42485-005 | Form: CREAM
Manufacturer: Biopelle, Inc.
Category: otc | Type: HUMAN OTC DRUG LABEL
Date: 20231212

ACTIVE INGREDIENTS: TITANIUM DIOXIDE 32 mg/1 mL; ZINC OXIDE 60 mg/1 mL
INACTIVE INGREDIENTS: WATER; ETHYLHEXYL PALMITATE; CYCLOMETHICONE 5; ALKYL (C12-15) BENZOATE; DIMETHICONE; POLYSORBATE 80; PEG-100 STEARATE; GLYCERYL MONOSTEARATE; PROPYLENE GLYCOL; CETYL ALCOHOL; SODIUM ACRYLATE/SODIUM ACRYLOYLDIMETHYLTAURATE COPOLYMER (4000000 MW); GLYCERIN; CYCLOMETHICONE 6; CAPRYLYL TRISILOXANE; ALUMINUM OXIDE; ISOHEXADECANE; BORON NITRIDE; SODIUM LEVULINATE; PHENOXYETHANOL; POLYHYDROXYSTEARIC ACID (2300 MW); SODIUM ANISATE; TRIETHOXYCAPRYLYLSILANE; PANTHENOL; IODOPROPYNYL BUTYLCARBAMATE; ALOE VERA LEAF; DMDM HYDANTOIN; ALLANTOIN; EDETATE SODIUM; METHYLPARABEN; ETHYLPARABEN; BUTYLPARABEN; BUTYLENE GLYCOL; PROPYLPARABEN; ISOBUTYLPARABEN; MATRICARIA CHAMOMILLA WHOLE; CAMELLIA SINENSIS WHOLE; FERRIC OXIDE RED

Broad Spectrum SPF 30 Up The Anti

Active Ingredients

Zinc Oxide 6.0% Titanium Dioxide 3.2%

Purpose

Sunscreen

Uses

- helps prevent sunburn
- if used as directed with other sun protections measures (see Directions), decreases the risk of skin cancer and early skin aging caused by the sun.

Warnings

For external use only

Do not use on damaged or broken skin

When using this product keep out of eyes. Rinse with water to remove.

Stop use and ask a doctor if rash occurs.

Keep out of reach of children.

If product is swallowed, get medical help or contact a Poison Control Center right away.

Directions

- apply to face and under throat after cleansing
- reapply:
-
  - after excessive perspiration
- Spending time in the sun increases your risk of skin cancer and early skin aging. To decrease this risk, regularly use a sunscreen with a broad spectrum SPF 15 or higher and other sun protection measures including: Sun Protection Measures.
-
  - limit time in the sun, especially from 10 a.m. - 2 p.m.
  - wear long sleeve shirts, pants, hats and sunglasses
- children under 6 months: Ask a doctor

Inactive Ingredients

water, ethylhexyl palmitate, cyclopentasiloxane, c12-15 alkyl benzoate, dimethicone, polysorbate 80, peg-100 stearate, glyceryl stearate, propylene glycol, polyglyceryl-6 isostearatem cetyl alcohol, sodium acrylate/sodium acryloyldimethyl laurate copolymer, glycerin, cyclohexasiloxane, caprylyl methicone, alumina, isohexadecane, boron nitride, triethoxysilylethyl polydimethylsiloxy hexyl dimethicone, sodium levulinate, lauryl peg-9 polydimethylsiloxyethyl dimethicone, acrylates/ammonium methacrylate copolymer, phenoxyethanol, polyhydroxystearic acid, sodium anisate, triethoxycaprylylsilane, panthenol, iodopropynyl butylcarbamate, dmdm hydantoin, aloe barbadensis leaf juice, allantoin, disodium edta, methylparaben, ethylparaben, butylparaben, butylene glycol, propylparaben, isobutylparaben, chamomilla recutita (matricaria) flower extract, camellia sinensis leaf extract, iron oxides.

Other Information

- protect this product from excessive heat and direct sun

Questions or comments?

Call toll free 1-866-424-6735 (weekdays)

PRESCRIBEDsolutions is Distributed By Biopelle, Inc.

A Ferndale Pharma Group Company, Ferndale, MI 48220

Made In USA